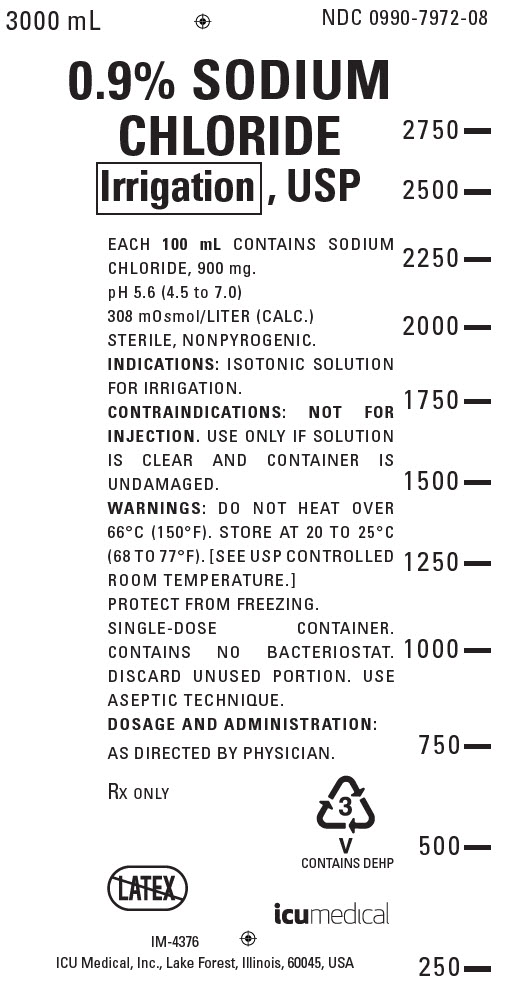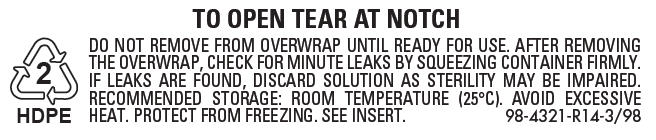 DRUG LABEL: Sodium Chloride
NDC: 0990-7972 | Form: IRRIGANT
Manufacturer: ICU Medical Inc.
Category: prescription | Type: HUMAN PRESCRIPTION DRUG LABEL
Date: 20251031

ACTIVE INGREDIENTS: SODIUM CHLORIDE 900 mg/100 mL
INACTIVE INGREDIENTS: WATER

0.9% Sodium Chloride Irrigation, USP

FOR ALL GENERAL IRRIGATION, RINSING, DILUTION AND CELL WASHING PURPOSES

Not For Injection By Usual Parenteral Routes

Flexible Irrigation Container

Rx only

DESCRIPTION

This product is a sterile, nonpyrogenic solution of electrolytes in water for injection intended only for sterile irrigation, rinsing, dilution and cell washing purposes.

Each 100 mL of 0.9% Sodium Chloride Irrigation, USP contains: Sodium chloride 900 mg. pH 5.6 (4.5 — 7.0). The solution is isotonic (308 mOsmol/liter, calc.) and has the following electrolyte content (mEq/liter): Na^+ 154; Cl¯ 154.

This irrigation solution contains no bacteriostat, antimicrobial agent or added buffer and is intended only for use as a single-dose, short procedure irrigation, or cell washing fluid. When smaller volumes are required the unused portion should be discarded.

It may be classified as a sterile irrigant, rinse, diluent, cell wash and pharmaceutical vehicle.

Sodium Chloride, USP is chemically designated NaCl, a white crystalline powder freely soluble in water.

Water for Injection, USP is chemically designated H2O.

The flexible plastic container is fabricated from a specially formulated polyvinylchloride. Water can permeate from inside the container into the overwrap but not in amounts sufficient to affect the solution significantly. Solutions in contact with the plastic container may leach out certain chemical components from the plastic in very small amounts; however, biological testing was supportive of the safety of the plastic container materials. Exposure to temperatures above 25°C/77°F during transport and storage will lead to minor losses in moisture content. Higher temperatures lead to greater losses. It is unlikely that these minor losses will lead to clinically significant changes within the expiration period.

CLINICAL PHARMACOLOGY

This irrigation solution exerts a mechanical cleansing action for sterile irrigation of body cavities, tissues or wounds, indwelling urethral catheters and surgical drainage tubes and for washing, rinsing or soaking surgical dressings, instruments and laboratory specimens. It also serves as a diluent or vehicle for drugs used for irrigation or other pharmaceutical preparations.

0.9% Sodium Chloride Irrigation, USP provides an isotonic saline irrigation identical in composition with 0.9% Sodium Chloride Injection, USP (normal saline).

0.9% Sodium Chloride Irrigation, USP is considered generally compatible with living tissues and organs.

Sodium chloride in water dissociates to provide sodium (Na^+) and chloride (Cl¯) ions. Sodium (Na^+) is the principal cation of the extracellular fluid and plays a large part in the therapy of fluid and electrolyte disturbances. Chloride (Cl¯) has an integral role in buffering action when oxygen and carbon dioxide exchange occurs in the red blood cells. The distribution and excretion of sodium (Na^+) and chloride (Cl¯) are largely under the control of the kidney which maintains a balance between intake and output.

Water is an essential constituent of all body tissues and accounts for approximately 70% of total body weight. Average normal adult daily requirements ranges from two to three liters (1.0 to 1.5 liters each for insensible water loss by perspiration and urine production).

Water balance is maintained by various regulatory mechanisms. Water distribution depends primarily on the concentration of electrolytes in the body compartments and sodium (Na^+) plays a major role in maintaining physiologic equilibrium.

INDICATIONS AND USAGE

This sterile, nonpyrogenic electrolyte solution is indicated for all general irrigation, washing, rinsing and dilution purposes including blood cell washing (when used in conjunction with automated intraoperative blood salvaging equipment).

CONTRAINDICATIONS

NOT FOR INJECTION BY USUAL PARENTERAL ROUTES.

An electrolyte solution should not be used for irrigation during electrosurgical procedures.

WARNINGS

FOR IRRIGATION ONLY. NOT FOR INJECTION.

Entry of a hypotonic solution into the circulation may cause hemolysis.

Irrigating fluids have been demonstrated to enter the systemic circulation in relatively large volumes; thus, each of these irrigations must be regarded as a systemic drug. Absorption of large amounts can cause fluid and/or solute overloading resulting in dilution of serum electrolyte concentrations, overhydration, congested states or pulmonary edema.

The risk of dilutional states is inversely proportional to the electrolyte concentrations of administered parenteral solutions. The risk of solute overload causing congested states with peripheral and pulmonary edema is directly proportional to the electrolyte concentrations of such solutions.

Do not heat over 66° C (150° F).

PRECAUTIONS

Do not use for irrigation that may result in absorption into the blood.

Aseptic technique is essential with the use of sterile solutions for irrigation of body cavities, wounds and urethral catheters or for wetting dressings that come in contact with body tissues or for cell washing techniques.

The flexible container is designed for use with nonvented irrigation sets or nonvented sets for cell washing harvesting systems. When used for irrigation via irrigation equipment, the administration set should be attached promptly. Unused portions should be discarded and a fresh container used for the start-up of each cycle or repeat procedure. For repeated irrigations of urethral catheters, a separate container should be used for each patient. When used for cell washing, the nonvented set should be attached promptly. The three liter container may be used to dispense new aliquots of washing solution for each wash cycle for the same patient. However, unused portions should be discarded and a separate container should be used for each patient and each start-up procedure.

Do not administer unless solution is clear, seal is intact and container is undamaged.

Discard unused portion.

Carcinogenesis, Mutagenesis, Impairment of Fertility: Studies with Sodium Chloride Irrigation, USP have not been performed to evaluate carcinogenic potential, mutagenic potential, or effects on fertility.

Nursing Mothers: Caution should be exercised when Sodium Chloride Irrigation, USP is administered to a nursing woman.

Pregnancy: Teratogenic Effects.

Pregnancy Category C. Animal reproduction studies have not been conducted with Sodium Chloride Irrigation, USP. It is also not known whether Sodium Chloride Irrigation, USP can cause fetal harm when administered to a pregnant woman or can affect reproduction capacity. This solution should be given to a pregnant woman only if clearly needed.

Pediatric Use: Safety and effectiveness of Sodium Chloride irrigation solution in pediatric patients have not been established by adequate and well-controlled trials. However, the use of Sodium Chloride irrigation solution in the pediatric population is referenced in the medical literature. The Warnings, Precautions, and Adverse Reactions identified in the label should be observed in the pediatric population.

Geriatric Use: An evaluation of current literature revealed no clinical experience identifying differences in response between elderly and younger patients.

This drug is known to be substantially secreted by the kidney, and the risk of toxic reactions to this drug may be greater in patients with impaired renal function. Because elderly patients are more likely to have decreased renal function, care should be taken in dose selection, and it may be useful to monitor renal function.

ADVERSE REACTIONS

Possible adverse effects arising from the irrigation of body cavities, tissues, cells or indwelling catheters and tubes are usually avoidable when proper procedures are followed. Displaced catheters or drainage tubes can lead to irrigation or infiltration of unintended structures or cavities. Excessive volume or pressure during irrigation of closed cavities may cause undue distension or disruption of tissues. Accidental contamination from careless technique may transmit infection.

Should any adverse reaction occur, discontinue the irrigant, evaluate the patient, institute appropriate therapeutic countermeasures and save the remainder of the fluid for examination if deemed necessary.

OVERDOSAGE

In the event of overhydration or solute overload, re-evaluate the patient and institute appropriate corrective measures. See WARNINGS, PRECAUTIONS and ADVERSE REACTIONS.

DOSAGE AND ADMINISTRATION

The dose is dependent upon the capacity or surface area of the structure to be irrigated and the nature of the procedure. When used as a diluent or vehicle for other drugs, the manufacturer's recommendations should be followed. For use in cell washing, the manufacturer's recommendations for blood salvaging and red cell processing should be followed.

Drug Interactions

Additives may be incompatible. Consult with pharmacist, if available. When introducing additives, use aseptic technique, mix thoroughly and do not store.

Parenteral drug products should be inspected visually for particulate matter and discoloration prior to administration, whenever solution container permits. See PRECAUTIONS.

HOW SUPPLIED

0.9% Sodium Chloride Irrigation, USP is supplied in a single-dose 3000 mL flexible irrigation container (NDC No. 0409-7972-08 / 0990-7972-08).

ICU Medical is transitioning NDC codes from "0409" to a "0990" labeler code. Both NDC codes are expected to be in the market for a period of time.

Store at 20 to 25°C (68 to 77°F). [See USP Controlled Room Temperature.] Protect from freezing.

Revised: June, 2018

EN-4661

ICU Medical, Inc., Lake Forest, Illinois, 60045, USA

PRINCIPAL DISPLAY PANEL - 3000 mL Bag Label

3000 mL
NDC 0990-7972-08

0.9% SODIUM
CHLORIDE
Irrigation , USP

EACH 100 mL CONTAINS SODIUM
CHLORIDE, 900 mg.
pH 5.6 (4.5 to 7.0)
308 mOsmol/LITER (CALC.)
STERILE, NONPYROGENIC.

INDICATIONS: ISOTONIC SOLUTION
FOR IRRIGATION.

CONTRAINDICATIONS: NOT FOR
INJECTION. USE ONLY IF SOLUTION
IS CLEAR AND CONTAINER IS
UNDAMAGED.

WARNINGS: DO NOT HEAT OVER
66°C (150°F). STORE AT 20 TO 25°C
(68 TO 77°F). [SEE USP CONTROLLED
ROOM TEMPERATURE.]
PROTECT FROM FREEZING.

SINGLE-DOSE CONTAINER.
CONTAINS NO BACTERIOSTAT.
DISCARD UNUSED PORTION. USE
ASEPTIC TECHNIQUE.

DOSAGE AND ADMINISTRATION:
AS DIRECTED BY PHYSICIAN.

RX ONLY

3
V
CONTAINS DEHP

icumedical

IM-4376

ICU Medical, Inc., Lake Forest, Illinois, 60045, USA

PRINCIPAL DISPLAY PANEL - 3000 mL Bag Overwrap

TO OPEN TEAR AT NOTCH

2
HDPE

DO NOT REMOVE FROM OVERWRAP UNTIL READY FOR USE. AFTER REMOVING
THE OVERWRAP, CHECK FOR MINUTE LEAKS BY SQUEEZING CONTAINER FIRMLY.
IF LEAKS ARE FOUND, DISCARD SOLUTION AS STERILITY MAY BE IMPAIRED.
RECOMMENDED STORAGE: ROOM TEMPERATURE (25°C). AVOID EXCESSIVE
HEAT. PROTECT FROM FREEZING. SEE INSERT.

98-4321-R14-3/98